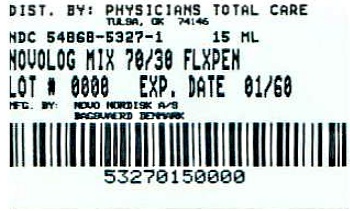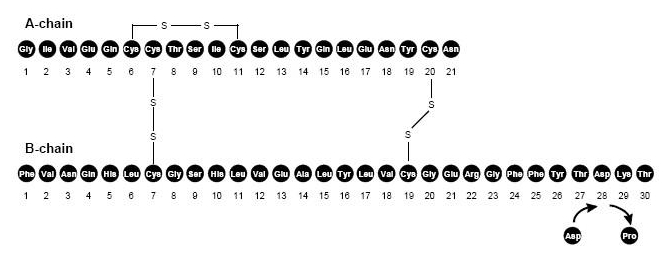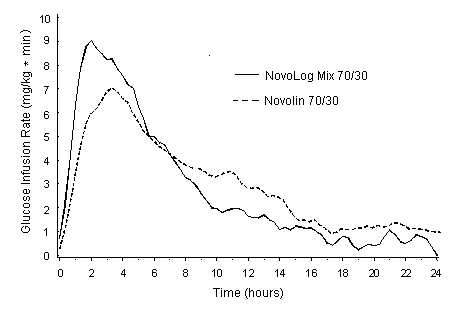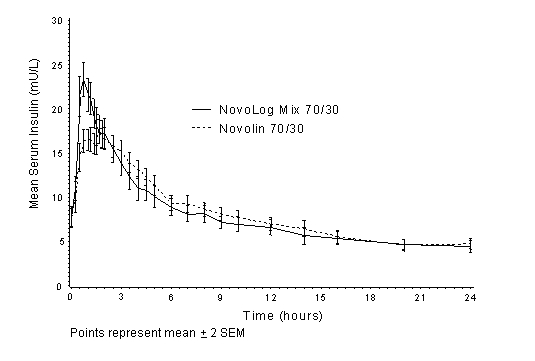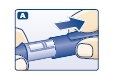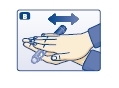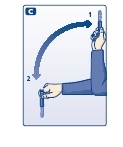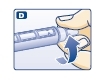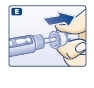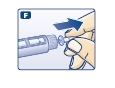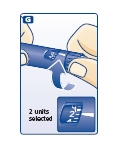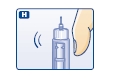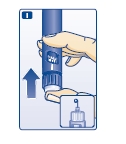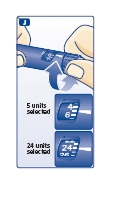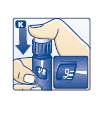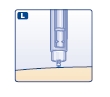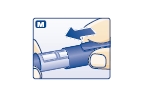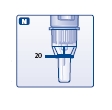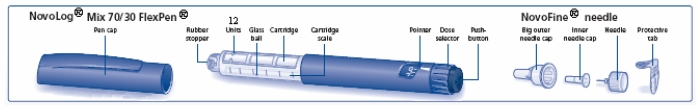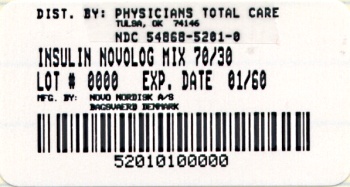 DRUG LABEL: NovoLog Mix 70/30
NDC: 54868-5201 | Form: INJECTION, SUSPENSION
Manufacturer: Physicians Total Care, Inc.
Category: prescription | Type: HUMAN PRESCRIPTION DRUG LABEL
Date: 20101108

ACTIVE INGREDIENTS: INSULIN ASPART 100 [iU]/1 mL
INACTIVE INGREDIENTS: SODIUM PHOSPHATE, DIBASIC, DIHYDRATE 1.25 mg/1 mL; HYDROCHLORIC ACID; MANNITOL 36.4 mg/1 mL; METACRESOL 1.72 mg/1 mL; PHENOL 1.5 mg/1 mL; PROTAMINE SULFATE 0.32 mg/1 mL; SODIUM CHLORIDE 0.58 mg/1 mL; SODIUM HYDROXIDE; ZINC 19.6 ug/1 mL

HIGHLIGHTS OF PRESCRIBING INFORMATION

These highlights do not include all the information needed to use NovoLog Mix 70/30 safely and effectively. See full prescribing information for NovoLog Mix 70/30. NovoLog® Mix 70/30 (70% insulin aspart protamine suspension and 30% insulin aspart injection, [rDNA origin]) Suspension for subcutaneous injection Initial U.S. Approval: 2001

RECENT MAJOR CHANGES

- Indications and Usage (1) 5/2010
- Dosage and Administration (2.1) 5/2010

1 INDICATIONS AND USAGE

NovoLog Mix 70/30 is an insulin analog indicated to improve glycemic control in patients with diabetes mellitus.

Important Limitations of Use: In premix insulins, such as Novolog Mix 70/30, the proportions of rapid acting and long acting insulins are fixed and do not allow for basal versus prandial dose adjustments (1).

2 DOSAGE AND ADMINISTRATION

- Only for subcutaneous injection (2.1)
  Type 1 DM: dose within 15 minutes before meal initiation.
  Type 2 DM: dose within 15 minutes before or after starting a meal.
- Do not administer intravenously (2.1).
- Do not use in insulin infusion pumps (2.1).
- Must be resuspended immediately before use (2.2).

3 DOSAGE FORMS AND STRENGTHS

Each presentation contains 100 Units of insulin aspart per mL (U-100) (3)

- 10 mL vials
- 3 mL NovoLog Mix 70/30 FlexPen

4 CONTRAINDICATIONS

- Do not use during episodes of hypoglycemia (4).
- Do not use in patients with hypersensitivity to NovoLog Mix 70/30 or one of its excipients (4).

5 WARNINGS AND PRECAUTIONS

- NovoLog Mix 70/30 should not be mixed with any other insulin product (5.1).
- Hypoglycemia is the most common adverse effect of insulin therapy. Glucose monitoring is recommended for all patients with diabetes. Any change of insulin dose should be made cautiously and only under medical supervision (5.1,5.2).
- Insulin, particularly when given in settings of poor glycemic control, can cause hypokalemia. Use caution in patients predisposed to hypokalemia (5.3).
- Like all insulins, NovoLog Mix 70/30 requirements may be reduced in patients with renal impairment or hepatic impairment (5.4, 5.5).
- Severe, life-threatening, generalized allergy, including anaphylaxis, may occur with insulin products, including NovoLog Mix 70/30 (5.6).

6 ADVERSE REACTIONS

Adverse reactions observed with insulin therapy include hypoglycemia, allergic reactions, local injection site reactions, lipodystrophy, rash and pruritus (6).

To report SUSPECTED ADVERSE REACTIONS, contact Novo Nordisk Inc. at 1-800-727-6500 or FDA at 1-800-FDA-1088 or www.fda.gov/medwatch

7 DRUG INTERACTIONS

- The following may increase the blood glucose lowering effect and susceptibility to hypoglycemia: oral antidiabetic products, pramlintide, ACE inhibitors, disopyramide, fibrates, fluoxetine, monoamine oxidase (MAO) inhibitors, propoxyphene, salicylates, somatostatin analog (e.g. octreotide), sulfonamide antibiotics (7).
- The following may reduce the blood-glucose-lowering effect: corticosteroids, niacin, danazol, diuretics, sympathomimetic agents (e.g., epinephrine, salbutamol, terbutaline), isoniazid, phenothiazine derivatives, somatropin, thyroid hormones, estrogens, progestogens (e.g., in oral contraceptives), atypical antipsychotics (7).
- Beta-blockers, clonidine, lithium salts, and alcohol may either potentiate or weaken the blood-glucose-lowering effect of insulin (7).
- Pentamidine may cause hypoglycemia, which may be followed by hyperglycemia (7).
- The signs of hypoglycemia may be reduced or absent in patients taking sympatholytic products such as beta-blockers, clonidine, guanethidine, and reserpine (7).

FULL PRESCRIBING INFORMATION

RECENT MAJOR CHANGES

Enter section text here

1 INDICATIONS AND USAGE

NovoLog Mix 70/30 is an insulin analog indicated to improve glycemic control in patients with diabetes mellitus.

Important Limitations of Use:

In premix insulins, such as Novolog Mix 70/30, the proportions of rapid acting and long acting insulins are fixed and do not allow for basal versus prandial dose adjustments.

2 DOSAGE AND ADMINISTRATION

Enter section text here

2.1 Dosing

NovoLog Mix 70/30 is an insulin analog with an earlier onset and intermediate duration of action in comparison to the basal human insulin premix. The addition of protamine to the rapid-acting aspart insulin analog (NovoLog) results in insulin activity that is 30% short-acting and 70% long-acting. NovoLog Mix 70/30 is typically dosed on a twice-daily basis (with each dose intended to cover 2 meals or a meal and a snack). The dosage of NovoLog Mix 70/30 must be individualized. The written prescription for NovoLog Mix 70/30 should include the full name, to avoid confusion with NovoLog (insulin aspart) and Novolin 70/30 (human premix).

NovoLog Mix 70/30 should appear uniformly white and cloudy. Do not use it if it looks clear or if it contains solid particles. NovoLog Mix 70/30 should not be used after the printed expiration date.

NovoLog Mix 70/30 should be administered by subcutaneous injection in the abdominal region, buttocks, thigh, or upper arm. NovoLog Mix 70/30 has a faster onset of action than human insulin premix 70/30 and should be dosed within 15 minutes before meal initiation for patients with type 1 diabetes. For patients with type 2 diabetes, dosing should occur within 15 minutes before or after meal initiation. Injection sites should be rotated within the same region to reduce the risk of lipodystrophy. As with all insulins, the duration of action may vary according to the dose, injection site, blood flow, temperature, and level of physical activity.

NovoLog Mix 70/30 should not be administered intravenously or used in insulin infusion pumps. Dose regimens of NovoLog Mix 70/30 will vary among patients and should be determined by the health care professional familiar with the patient’s recommended glucose treatment goals, metabolic needs, eating habits, and other lifestyle variables.

2.2 Resuspension

NovoLog Mix 70/30 is a suspension that must be visually inspected and resuspended immediately before use. The NovoLog Mix 70/30 vial should be rolled gently in your hands in a horizontal position 10 times to mix it. The rolling procedure must be repeated until the suspension appears uniformly white and cloudy. Inject immediately. Resuspension is easier when the insulin has reached room temperature.

The NovoLog Mix 70/30 FlexPen should be rolled 10 times gently between your hands in a horizontal position. Thereafter, turn the NovoLog Mix 70/30 FlexPen upside down so that the glass ball moves from one end of the reservoir to the other. Do this at least 10 times. The rolling and turning procedure must be repeated until the suspension appears uniformly white and cloudy. Inject immediately. Before each subsequent injection, turn the disposable NovoLog Mix 70/30 FlexPen upside down so that the glass ball moves from one end of the reservoir to the other at least 10 times and until the suspension appears uniformly white and cloudy. Inject immediately.

3 DOSAGE FORMS AND STRENGTHS

NovoLog Mix 70/30 is available in the following package sizes: each presentation contains 100 units of insulin aspart per mL (U-100).

- 10 mL vials
- 3 mL NovoLog Mix 70/30 FlexPen

4 CONTRAINDICATIONS

NovoLog Mix 70/30 is contraindicated

- during episodes of hypoglycemia
- in patients with hypersensitivity to NovoLog Mix 70/30 or one of its excipients.

5 WARNINGS AND PRECAUTIONS

Enter section text here

5.1 Administration

The short and long-acting components of insulin mixes, including NovoLog Mix 70/30, cannot be titrated independently. Because NovoLog Mix 70/30 has peak pharmacodynamic activity between 1-4 hours after injection, it should be administered within 15 minutes of meal initiation [see Clinical Pharmacology (12)]. The dose of insulin required to provide adequate glycemic control for one of the meals may result in hyper- or hypoglycemia for the other meal. The pharmacodynamic profile may also be inadequate for patients who require more frequent meals.

NovoLog Mix 70/30 should not be mixed with any other insulin product.

NovoLog Mix 70/30 should not be used intravenously.

NovoLog Mix 70/30 should not be used in insulin infusion pumps.

Glucose monitoring is recommended for all patients with diabetes. Any change of insulin dose should be made cautiously and only under medical supervision. Changing from one insulin product to another or changing the insulin strength may result in the need for a change in dosage. Changes may also be necessary during illness, emotional stress, and other physiologic stress in addition to changes in meals and exercise.

The pharmacokinetic and pharmacodynamic profiles of all insulins may be altered by the site used for injection and the degree of vascularization of the site. Smoking, temperature, and exercise contribute to variations in blood flow and insulin absorption. These and other factors contribute to inter- and intra-patient variability.

Needles and NovoLog Mix 70/30 FlexPen must not be shared.

5.2 Hypoglycemia

Hypoglycemia is the most common adverse effect of insulin therapy, including NovoLog Mix 70/30. Severe hypoglycemia may lead to unconsciousness and/or convulsions and may result in temporary or permanent impairment of brain function or even death. Severe hypoglycemia requiring the assistance of another person and/or parenteral glucose infusion or glucagon administration has been observed in clinical trials with insulin, including trials with NovoLog Mix 70/30.

The timing of hypoglycemia may reflect the time-action profile of the insulin formulation [see Clinical Pharmacology (12)]. Other factors, such as changes in dietary intake (e.g., amount of food or timing of meals), injection site, exercise, and concomitant medications may also alter the risk of hypoglycemia [see Drug Interactions (7)]. As with all insulins, use caution in patients with hypoglycemia unawareness and in patients who may be predisposed to hypoglycemia (e.g. patients who are fasting or have erratic food intake). The patient’s ability to concentrate and react may be impaired as a result of hypoglycemia. This may present a risk in situations where these abilities are especially important, such as driving or operating machinery.

Rapid changes in serum glucose levels may induce symptoms of hypoglycemia in persons with diabetes, regardless of the glucose value. Early warning symptoms of hypoglycemia may be different or less pronounced under certain conditions, such as long duration of diabetes, diabetic nerve disease, use of medications such as beta-blockers, or intensified diabetes control [see Drug Interactions (7)].

5.3 Hypokalemia

All insulin products, including NovoLog Mix 70/30, cause a shift in potassium from the extracellular to intracellular space, possibly leading to hypokalemia that, if left untreated, may cause respiratory paralysis, ventricular arrhythmia, and death. Use caution in patients who may be at risk for hypokalemia (e.g. patients using potassium-lowering medications or patients taking medications sensitive to potassium concentrations).

5.4 Renal Impairment

Clinical or pharmacology studies with NovoLog Mix 70/30 in diabetic patients with various degrees of renal impairment have not been conducted. As with other insulins, the requirements for NovoLog Mix 70/30 may be reduced in patients with renal impairment [see Clinical Pharmacology (12.3)].

5.5 Hepatic Impairment

Clinical or pharmacology studies with NovoLog Mix 70/30 in diabetic patients with various degrees of hepatic impairment have not been conducted. As with other insulins, the requirements for NovoLog Mix 70/30 may be reduced in patients with hepatic impairment [see Clinical Pharmacology (12.3)].

5.6 Hypersensitivity and Allergic Reactions

Local Reactions- As with other insulin therapy, patients may experience reactions such as erythema, edema or pruritus at the site of NovoLog Mix 70/30 injection. These reactions usually resolve in a few days to a few weeks, but in some occasions, may require discontinuation of NovoLog Mix 70/30. In some instances, these reactions may be related to the insulin molecule, other components in the insulin preparation including protamine and cresol, components in skin cleansing agents, or injection techniques. Localized reactions and generalized myalgias have been reported with the use of cresol as an injectable excipient.

Systemic Reactions- Less common, but potentially more serious, is generalized allergy to insulin, which may cause rash (including pruritus) over the whole body, shortness of breath, wheezing, reduction in blood pressure, rapid pulse, or sweating. Severe cases of generalized allergy, including anaphylactic reaction, may be life threatening.

5.7 Antibody Production

Specific anti-insulin antibodies as well as cross-reacting anti-insulin antibodies were monitored in a 3-month, open-label comparator trial as well as in a long-term extension trial. Changes in cross-reactive antibodies were more common after NovoLog Mix 70/30 than with Novolin 70/30 but these changes did not correlate with change in HbA1c or increase in insulin dose. The clinical significance of these antibodies has not been established. Antibodies did not increase further after long-term exposure (>6 months) to NovoLog Mix 70/30.

6 ADVERSE REACTIONS

Clinical Trial Experience

Clinical trials are conducted under widely varying designs, therefore, the adverse reaction rates reported in one clinical trial may not be easily compared to those rates reported in another clinical trial, and may not reflect the rates actually observed in clinical practice.

- Hypoglycemia

Hypoglycemia is the most commonly observed adverse reaction in patients using insulin, including NovoLog Mix 70/30 [see Warnings and Precautions (5.2)]. NovoLog Mix 70/30 should not be used during episodes of hypoglycemia [see Contraindications (4)] and [Warnings and Precautions (5)].

- Insulin initiation and glucose control intensification

Intensification or rapid improvement in glucose control has been associated with transitory, reversible ophthalmologic refraction disorder, worsening of diabetic retinopathy, and acute painful peripheral neuropathy. However, long-term glycemic control decreases the risk of diabetic retinopathy and neuropathy.

- Lipodystrophy

Long-term use of insulin, including NovoLog Mix 70/30, can cause lipodystrophy at the site of repeated insulin injections. Lipodystrophy includes lipohypertrophy (thickening of adipose tissue) and lipoatrophy (thinning of adipose tissue), and may affect insulin absorption. Rotate insulin injection sites within the same region to reduce the risk of lipodystrophy.

- Weight gain

Weight gain can occur with some insulin therapies, including NovoLog Mix 70/30, and has been attributed to the anabolic effects of insulin and the decrease in glycosuria.

- Peripheral Edema

Insulin may cause sodium retention and edema, particularly if previously poor metabolic control is improved by intensified insulin therapy.

- Frequencies of adverse drug reactions

The frequencies of adverse drug reactions during a clinical trial with NovoLog Mix 70/30 in patients with type 1 diabetes mellitus and type 2 diabetes mellitus are listed in the tables below. The trial was a three-month, open-label trial in patients with Type 1 or Type 2 diabetes who were treated twice daily (before breakfast and before supper) with NovoLog Mix 70/30.

Table 1: Treatment-Emergent Adverse Events in Patients with Type 1 diabetes mellitus (Adverse events with frequency ≥ 5% are included.)
 | NovoLog Mix 70/30; (N=55) | Novolin 70/30; (N=49)
Preferred Term | N | % | N | %
Hypoglycemia | 38 | 69 | 37 | 76
Headache | 19 | 35 | 6 | 12
Influenza-like symptoms | 7 | 13 | 1 | 2
Dyspepsia | 5 | 9 | 3 | 6
Back pain | 4 | 7 | 2 | 4
Diarrhea | 4 | 7 | 3 | 6
Pharyngitis | 4 | 7 | 1 | 2
Rhinitis | 3 | 5 | 6 | 12
Skeletal pain | 3 | 5 | 2 | 4
Upper respiratory tract infection | 3 | 5 | 1 | 2

Table 2: Treatment-Emergent Adverse Events in Patients with Type 2 diabetes mellitus (Adverse events with frequency ≥ 5% are included.)
 | NovoLog Mix 70/30; (N=85) | Novolin 70/30; (N=102)
Preferred Term | N | % | N | %
Hypoglycemia | 40 | 47 | 51 | 50
Upper respiratory tract infection | 10 | 12 | 6 | 6
Headache | 8 | 9 | 8 | 8
Diarrhea | 7 | 8 | 2 | 2
Neuropathy | 7 | 8 | 2 | 2
Pharyngitis | 5 | 6 | 4 | 4
Abdominal pain | 4 | 5 | 0 | 0
Rhinitis | 4 | 5 | 2 | 2

Postmarketing Data

Additional adverse reactions have been identified during post-approval use of NovoLog Mix 70/30. Because these adverse reactions are reported voluntarily from a population of uncertain size, it is generally not possible to reliably estimate their frequency. They include medication errors in which other insulins have been accidentally substituted for NovoLog Mix 70/30 [see Patient Counseling Information (17)].

7 DRUG INTERACTIONS

A number of substances affect glucose metabolism and may require insulin dose adjustment and particularly close monitoring.

- The following are examples of substances that may increase the blood-glucose-lowering effect and susceptibility to hypoglycemia: oral antidiabetic products, pramlintide, ACE inhibitors, disopyramide, fibrates, fluoxetine, monoamine oxidase (MAO) inhibitors, propoxyphene, salicylates, somatostatin analog (e.g. octreotide), sulfonamide antibiotics.
- The following are examples of substances that may reduce the blood-glucose-lowering effect: corticosteroids, niacin, danazol, diuretics, sympathomimetic agents (e.g., epinephrine, salbutamol, terbutaline), isoniazid, phenothiazine derivatives, somatropin, thyroid hormones, estrogens, progestogens (e.g., in oral contraceptives), atypical antipsychotics.
- Beta-blockers, clonidine, lithium salts, and alcohol may either potentiate or weaken the blood-glucose-lowering effect of insulin.
- Pentamidine may cause hypoglycemia, which may sometimes be followed by hyperglycemia.
- The signs of hypoglycemia may be reduced or absent in patients taking sympatholytic products such as beta-blockers, clonidine, guanethidine, and reserpine.

8 USE IN SPECIFIC POPULATIONS

Enter section text here

8.1 Pregnancy

Pregnancy Category B.

All pregnancies have a background risk of birth defects, loss, or other adverse outcome regardless of drug exposure. This background risk is increased in pregnancies complicated by hyperglycemia and may be decreased with good metabolic control. It is essential for patients with diabetes or history of gestational diabetes to maintain good metabolic control before conception and throughout pregnancy. Insulin requirements may decrease during the first trimester, generally increase during the second and third trimesters, and rapidly decline after delivery. Careful monitoring of glucose control is essential in such patients.

An open-label, randomized study compared the safety and efficacy of NovoLog (the rapid-acting component of NovoLog Mix 70/30) versus human insulin in the treatment of pregnant women with Type 1 diabetes (322 exposed pregnancies (NovoLog: 157, human insulin: 165)). Two-thirds of the enrolled patients were already pregnant when they entered the study. Since only one-third of the patients enrolled before conception, the study was not large enough to evaluate the risk of congenital malformations. Mean HbA1c of ~ 6% was observed in both groups during pregnancy, and there was no significant difference in the incidence of maternal hypoglycemia.

Animal reproduction studies have not been conducted with NovoLog Mix 70/30. However, subcutaneous reproduction and teratology studies have been performed with NovoLog (the rapid-acting component of NovoLog Mix 70/30) and regular human insulin in rats and rabbits. In these studies, NovoLog was given to female rats before mating, during mating, and throughout pregnancy, and to rabbits during organogenesis. The effects of NovoLog did not differ from those observed with subcutaneous regular human insulin.

NovoLog, like human insulin, caused pre- and post-implantation losses and visceral/skeletal abnormalities in rats at a dose of 200 U/kg/day (approximately 32-times the human subcutaneous dose of 1.0 U/kg/day, based on U/body surface area), and in rabbits at a dose of 10 U/kg/day (approximately three times the human subcutaneous dose of 1.0 U/kg/day, based on U/body surface area). The effects are probably secondary to maternal hypoglycemia at high doses. No significant effects were observed in rats at a dose of 50 U/kg/day and rabbits at a dose of 3 U/kg/day. These doses are approximately 8 times the human subcutaneous dose of 1.0 U/kg/day for rats and equal to the human subcutaneous dose of 1.0 U/kg/day for rabbits based on U/body surface area.

Female patients should be advised to discuss with their physician if they intend to, or if they become pregnant. There are no adequate and well-controlled studies of the use of NovoLog Mix 70/30 in pregnant women.

8.2 Nursing Mothers

It is unknown whether insulin aspart is excreted in human milk as occurs with human insulin. There are no adequate and well-controlled studies of the use of NovoLog Mix 70/30 or NovoLog in lactating women. Women with diabetes who are lactating may require adjustments of their insulin doses.

8.4 Pediatric Use

Safety and effectiveness of NovoLog Mix 70/30 have not been established in pediatric patients.

8.5 Geriatric Use

Clinical studies of NovoLog Mix 70/30 did not include sufficient numbers of patients aged 65 and over to determine whether they respond differently than younger patients. In general, dose selection for an elderly patient should be cautious, usually starting at the low end of the dosing range reflecting the greater frequency of decreased hepatic, renal, or cardiac function, and of concomitant disease or other drug therapy in this population.

10 OVERDOSAGE

Hypoglycemia may occur as a result of an excess of insulin relative to food intake, energy expenditure, or both. Mild episodes of hypoglycemia usually can be treated with oral glucose. Adjustments in drug dosage, meal patterns, or exercise, may be needed. More severe episodes with coma, seizure, or neurologic impairment may be treated with intramuscular/subcutaneous glucagon or concentrated intravenous glucose. Sustained carbohydrate intake and observation may be necessary because hypoglycemia may recur after apparent clinical recovery.

11 DESCRIPTION

NovoLog Mix 70/30 (70% insulin aspart protamine suspension and 30% insulin aspart injection, [rDNA origin]) is a human insulin analog suspension containing 70% insulin aspart protamine crystals and 30% soluble insulin aspart. NovoLog Mix 70/30 is a blood glucose-lowering agent with an earlier onset and an intermediate duration of action. Insulin aspart is homologous with regular human insulin with the exception of a single substitution of the amino acid proline by aspartic acid in position B28, and is produced by recombinant DNA technology utilizing Saccharomyces cerevisiae (baker’s yeast). Insulin aspart (NovoLog) has the empirical formula C256H381N65O79S6 and a molecular weight of 5825.8 Da.

Figure 1. Structural formula of insulin aspart

NovoLog Mix 70/30 is a uniform, white, sterile suspension that contains insulin aspart 100 Units/mL.

Inactive ingredients for the 10 mL vial are mannitol 36.4 mg/mL, phenol 1.50 mg/mL, metacresol 1.72 mg/mL, zinc 19.6 μg/mL, disodium hydrogen phosphate dihydrate 1.25 mg/mL, sodium chloride 0.58 mg/mL, and protamine sulfate 0.32 mg/mL.

Inactive ingredients for the NovoLog Mix 70/30 FlexPen are glycerol 16.0 mg/mL, phenol 1.50 mg/mL, metacresol 1.72 mg/mL, zinc 19.6 μg/mL, disodium hydrogen phosphate dihydrate 1.25 mg/mL, sodium chloride 0.877 mg/mL, and protamine sulfate 0.32 mg/mL. NovoLog Mix 70/30 has a pH of 7.20 - 7.44. Hydrochloric acid or sodium hydroxide may be added to adjust pH.

12 CLINICAL PHARMACOLOGY

Enter section text here

12.1 Mechanism of Action

The primary activity of NovoLog Mix 70/30 is the regulation of glucose metabolism. Insulins, including NovoLog Mix 70/30, bind to the insulin receptors on muscle, liver and fat cells and lower blood glucose by facilitating the cellular uptake of glucose and simultaneously inhibiting the output of glucose from the liver.

12.2 Pharmacodynamics

The two euglycemic clamp studies described below [see Clinical Pharmacology (12.3)] assessed glucose utilization after dosing of healthy volunteers. NovoLog Mix 70/30 has an earlier onset of action than human premix 70/30 in studies of normal volunteers and patients with diabetes. The onset of action is between 10-20 minutes for NovoLog Mix 70/30 compared to 30 minutes for Novolin 70/30. The mean ± SD time to peak activity for NovoLog Mix 70/30 is 2.4 hr ± 0.8hr compared to 4.2 hr ± 0.4 hr for Novolin 70/30. The duration of action may be as long as 24 hours (see Figure 2).

Figure 2. Pharmacodynamic Activity Profile of NovoLog Mix 70/30 and Novolin 70/30 in healthy subjects.

12.3 Pharmacokinetics

The single substitution of the amino acid proline with aspartic acid at position B28 in insulin aspart (NovoLog) reduces the molecule’s tendency to form hexamers as observed with regular human insulin. The rapid absorption characteristics of NovoLog are maintained by NovoLog Mix 70/30. The insulin aspart in the soluble component of NovoLog Mix 70/30 is absorbed more rapidly from the subcutaneous layer than regular human insulin. The remaining 70% is in crystalline form as insulin aspart protamine which has a prolonged absorption profile after subcutaneous injection.

Bioavailability and Absorption- The relative bioavailability of NovoLog Mix 70/30 compared to NovoLog and Novolin 70/30 indicates that the insulins are absorbed to similar extent. In euglycemic clamp studies in healthy volunteers (n=23) after dosing with NovoLog Mix 70/30 (0.2 U/kg), a mean maximum serum concentration (Cmax) of 23.4 ± 5.3 mU/L was reached after 60 minutes. The mean half-life (t1/2) of NovoLog Mix 70/30 was about 8 to 9 hours. Serum insulin levels returned to baseline 15 to 18 hours after a subcutaneous dose of NovoLog Mix 70/30. Similar data were seen in a separate euglycemic clamp study in healthy volunteers (n=24) after dosing with NovoLog Mix 70/30 (0.3 U/kg). A Cmax of 61.3 ± 20.1 mU/L was reached after 85 minutes. Serum insulin levels returned to baseline 12 hours after a subcutaneous dose.

The Cmax and the area under the insulin concentration-time curve (AUC) after administration of NovoLog Mix 70/30 was approximately 20% greater than those after administration of Novolin 70/30, (see Fig. 3 for pharmacokinetic profiles).

Figure 3. Pharmacokinetic Profiles of NovoLog Mix 70/30 and Novolin 70/30

Distribution and Elimination- NovoLog has a low binding to plasma proteins, 0 to 9%, similar to regular human insulin. After subcutaneous administration in normal male volunteers (n=24), NovoLog was more rapidly eliminated than regular human insulin with an average apparent half-life of 81 minutes compared to 141 minutes for regular human insulin.

The effect of sex, age, obesity, ethnic origin, renal and hepatic impairment, pregnancy, or smoking, on the pharmacodynamics and pharmacokinetics of NovoLog Mix 70/30 has not been studied.

13 NONCLINICAL TOXICOLOGY

Enter section text here

13.1 Carcinogenesis, Mutagenesis, Impairment of Fertility

Standard 2-year carcinogenicity studies in animals have not been performed to evaluate the carcinogenic potential of NovoLog Mix 70/30. In 52-week studies, Sprague-Dawley rats were dosed subcutaneously with NovoLog, the rapid-acting component of NovoLog Mix 70/30, at 10, 50, and 200 U/kg/day (approximately 2, 8, and 32 times the human subcutaneous dose of 1.0 U/kg/day, based on U/body surface area, respectively). At a dose of 200 U/kg/day, NovoLog increased the incidence of mammary gland tumors in females when compared to untreated controls. The incidence of mammary tumors found with NovoLog was not significantly different from that found with regular human insulin. The relevance of these findings to humans is not known.

NovoLog was not genotoxic in the following tests: Ames test, mouse lymphoma cell forward gene mutation test, human peripheral blood lymphocyte chromosome aberration test, in vivo micronucleus test in mice, and in ex vivo UDS test in rat liver hepatocytes.

In fertility studies in male and female rats, NovoLog at subcutaneous doses up to 200 U/kg/day (approximately 32 times the human subcutaneous dose, based on U/body surface area) had no direct adverse effects on male and female fertility, or on general reproductive performance of animals.

13.2 Animal Toxicology and/or Pharmacology

In standard biological assays in mice and rabbits, one unit of NovoLog has the same glucose-lowering effect as one unit of regular human insulin. However, the effect of NovoLog Mix 70/30 is more rapid in onset compared to Novolin (human insulin) 70/30 due to its faster absorption after subcutaneous injection.

14 CLINICAL STUDIES

Enter section text here

14.1 NovoLog Mix 70/30 versus Novolin 70/30

In a three-month, open-label trial, patients with Type 1 (n=104) or Type 2 (n=187) diabetes were treated twice daily (before breakfast and before supper) with NovoLog Mix 70/30 or Novolin 70/30. Patients had received insulin for at least 24 months before the study. Oral hypoglycemic agents were not allowed within 1 month prior to the study or during the study. The small changes in HbA1c were comparable across the treatment groups (see Table 3).

Table 3: Glycemic Parameters at the End of Treatment [Mean ± SD (N subjects)]
 | NovoLog Mix 70/30 | Novolin 70/30
Type 1, N=104
Fasting Blood Glucose (mg/dL) | 174 ± 64 (48) | 142 ± 59 (44)
1.5 Hour Post Breakfast (mg/dL) | 187 ± 82 (48) | 200 ± 82 (42)
1.5 Hour Post Dinner (mg/dL) | 162 ± 77 (47) | 171 ± 66 (41)
HbA1c (%) Baseline | 8.4 ± 1.2 (51) | 8.5 ± 1.1 (46)
HbA1c (%) Week 12 | 8.4 ± 1.1 (51) | 8.3 ± 1.0 (47)
Type 2, N=187
Fasting Blood Glucose (mg/dL) | 153 ± 40 (76) | 152 ± 69 (93)
1.5 Hour Post Breakfast (mg/dL) | 182 ± 65 (75) | 200 ± 80 (92)
1.5 Hour Post Dinner (mg/dL) | 168 ± 51 (75) | 191 ± 65 (93)
HbA1c (%) Baseline | 8.1 ± 1.2 (82) | 8.2 ± 1.3 (98)
HbA1c (%) Week 12 | 7.9 ± 1.0 (81) | 8.1 ± 1.1 (96)

The significance, with respect to the long-term clinical sequelae of diabetes, of the differences in postprandial hyperglycemia between treatment groups has not been established.

Specific anti-insulin antibodies as well as cross-reacting anti-insulin antibodies were monitored in the 3-month, open-label comparator trial as well as in a long-term extension trial.

14.2 Combination Therapy: Insulin and Oral Agents in Patients with Type 2 Diabetes

Trial 1:

In a 34-week, open-label trial, insulin-naïve patients with type 2 diabetes currently treated with 2 oral antidiabetic agents were switched to treatment with metformin and pioglitazone. During an 8-week optimization period metformin and pioglitazone were increased to 2500 mg per day and 30 or 45 mg per day, respectively. After the optimization period, subjects were randomized to receive either NovoLog Mix 70/30 twice daily added on to the metformin and pioglitazone regimen or continue the current optimized metformin and pioglitazone therapy. NovoLog Mix 70/30 was started at a dose of 6 IU twice daily (before breakfast and before supper). Insulin doses were titrated to a pre-meal glucose goal of 80-110 mg/dL. The total daily insulin dose at the end of the study was 56.9 ± 30.5 IU.

Table 4: Combination Therapy with Oral Agents and Insulin in Patients with Type 2 Diabetes Mellitus [Mean (SD)]
Treatment duration 24-weeks | NovoLog Mix 70/30 + Metformin; + Pioglitazone | Metformin + Pioglitazone
HbA1c
Baseline mean ± SD (n) | 8.1 ± 1.0 (102) | 8.1 ± 1.0 (98)
End-of-study mean ± SD (n) - LOCF | 6.6 ± 1.0 (93) | 7.8 ± 1.2 (87)
Adjusted Mean change from baseline ± SE (n)* | -1.6 ± 0.1 (93) | -0.3 ± 0.1 (87)
Treatment difference mean ± SE* 95% CI* | -1.3 ± 0.1; (-1.6, -1.0)
Percentage of subjects reaching HbA1c <7.0% | 76% | 24%
Percentage of subjects reaching HbA1c<6.5% | 59% | 12%
Fasting Blood Glucose (mg/dL)
Baseline Mean ± SD (n) | 173 ± 39.8 (93) | 163 ± 35.4 (88)
End of Study Mean ± SD (n) - LOCF | 130 ± 50.0 (90) | 162 ± 40.8 (84)
Adjusted Mean change from baseline ± SE (n)* | -43.0 ± 5.3 (90) | -3.9 ± 5.3 (84)
End-of-Study Blood Glucose (Plasma) (mg/dL)
2 Hour Post Breakfast | 138 ± 42.8 (86) | 188 ± 57.7 (74)
2 Hour Post Lunch | 150 ± 41.5 (86) | 176 ± 56.5 (74)
2 Hour Post Dinner | 141 ± 57.8 (86) | 195 ± 60.1 (74)
% of patients with severe hypoglycemia** | 3 | 0
% of patients with minor hypoglycemia** | 52 | 3
Weight gain at end of study (kg)** | 4.6 ± 4.3 (92) | 0.8 ± 3.2 (86)

*Adjusted mean per group, treatment difference, and 95% CI were obtained based on an ANCOVA model with treatment, FPG stratum, and secretagogue stratum as fixed factors and baseline HbA1c as the covariate.

**If metabolic control is improved by intensified insulin therapy, an increased risk of hypoglycemia and weight gain may occur.

Trial 2:

In a 28-week, open-label trial, insulin-naïve patients with type 2 diabetes with fasting plasma glucose above 140 mg/dL currently treated with metformin ± thiazolidinedione therapy were randomized to receive either NovoLog Mix 70/30 twice daily [before breakfast and before supper] or insulin glargine once daily^1 (see Table 5). NovoLog Mix 70/30 was started at an average dose of 5-6 IU (0.07 ± 0.03 IU/kg) twice daily (before breakfast and before supper), and bedtime insulin glargine was started at 10-12 IU (0.13 ± 0.03 IU/kg). Insulin doses were titrated weekly by decrements or increments of -2 to +6 units per injection to a pre-meal glucose goal of 80-110 mg/dL. The metformin dose was adjusted to 2550 mg/day. Approximately one-third of the patients in each group were also treated with pioglitazone (30 mg/day). Insulin secretagogues were discontinued in order to reduce the risk of hypoglycemia. Most patients were Caucasian (53%), and the mean initial weight was 90 kg.

Table 5: Combination Therapy with Oral Agents and Two Types of Insulin in Patients with Type 2 Diabetes Mellitus [Mean (SD)]
Treatment duration 28-weeks | NovoLog Mix 70/30 + Metformin ± Pioglitazone | Insulin Glargine + Metformin ± Pioglitazone
Number of patients | 117 | 116
HbA1c
Baseline mean (%) | 9.7 ± 1.5 (117) | 9.8 ± 1.4 (114)
End-of-study mean (± SD) | 6.9 ± 1.2 (108) | 7.4 ± 1.2 (114)
Mean change from baseline | -2.7 ± 1.6 (108) | -2.4 ± 1.5 (114)
Percentage of subjects reaching HbA1c <7.0% | 66% | 40%
Total Daily Insulin Dose at end of study (U) | 78 ± 40 (117) | 51 ± 27 (116)
% of patients with severe hypoglycemia | 0 | 0
% of minor hypoglycemia | 43 | 16
Weight gain at end of study | 5.4 ± 4.8 (117) | 3.5 ± 4.5 (116)

15 REFERENCES

1. Raskin R, Allen E, Hollander P, et al. Initiating insulin therapy in type 2 diabetes: a comparison of biphasic and basal insulin analogs. Diabetes Care. 2005; 28:260-265.

16 HOW SUPPLIED/STORAGE AND HANDLING

Enter section text here

16.1 How Supplied

NovoLog Mix 70/30 is available in the following package sizes: each presentation contains 100 Units of insulin aspart per mL (U-100).

10 mL vials | NDC 54868-5201-0
3 mL NovoLog Mix 70/30 FlexPen | NDC 54868-5327-1

NovoLog Mix 70/30 vials and NovoLog Mix 70/30 FlexPen are latex free.

16.2 Recommended Storage

Unused NovoLog Mix 70/30 should be stored in a refrigerator between 2°C and 8°C (36°F to 46°F). Do not store in the freezer or directly adjacent to the refrigerator cooling element. Do not freeze NovoLog Mix 70/30 or use NovoLog Mix 70/30 if it has been frozen.

Vials: After initial use, a vial may be kept at temperatures below 30°C (86°F) for up to 28 days, but should not be exposed to excessive heat or sunlight. Open vials may be refrigerated.

Unpunctured vials can be used until the expiration date printed on the label if they are stored in a refrigerator. Keep unused vials in the carton so they will stay clean and protected from light.

NovoLog Mix 70/30 FlexPen: Once a NovoLog Mix 70/30 FlexPen is punctured, it should be kept at temperatures below 30°C (86°F) for up to 14 days, but should not be exposed to excessive heat or sunlight. A NovoLog Mix 70/30 FlexPen in use must NOT be stored in the refrigerator. Keep the disposable NovoLog Mix 70/30 FlexPen away from direct heat and sunlight. An unpunctured NovoLog Mix 70/30 FlexPen can be used until the expiration date printed on the label if they are stored in a refrigerator. Keep any unused NovoLog Mix 70/30 FlexPen in the carton so it will stay clean and protected from light.

These storage conditions are summarized in the following table:

 | Not in-use (unopened); Room Temperature; (below 30°C[86°F]) | Not in-use (unopened); Refrigerated; (2°C - 8°C [36°F- 46°F]) | In-use (opened); Room Temperature; (below 30°C[86°F])
10 mL vial | 28 days | Until expiration date | 28 days (refrigerated/room temperature)
3mL NovoLog Mix 70/30 FlexPen | 14 days | Until expiration date | 14 days (Do not refrigerate

17 PATIENT COUNSELING INFORMATION

[see FDA-Approved Patient Labeling]

17.1 Physicians Instructions

Maintenance of normal or near-normal glucose control is a treatment goal in diabetes mellitus and has been associated with a reduction in diabetic complications. Patients should be informed about potential risks and advantages of NovoLog Mix 70/30 therapy including the possible adverse reactions. Patients should also be offered continued education and advice on insulin therapies, injection technique, life-style management, regular glucose monitoring, periodic glycosylated hemoglobin testing, recognition and management of hypo- and hyperglycemia, adherence to meal planning, complications of insulin therapy, timing of dose, instruction for use of injection devices, and proper storage of insulin. See Patient Information supplied with the product. Patients should be informed that frequent, patient-performed blood glucose measurements are needed to achieve optimal glycemic control and avoid both hyper- and hypoglycemia, and diabetic ketoacidosis.

The patient’s ability to concentrate and react may be impaired as a result of hypoglycemia. This may present a risk in situations where these abilities are especially important, such as driving or operating other machinery. Patients who have frequent hypoglycemia or reduced or absent warning signs of hypoglycemia should be advised to use caution when driving or operating machinery.

Accidental substitutions between NovoLog Mix 70/30 and other insulin products have been reported. Patients should be instructed to always carefully check that they are administering the appropriate insulin to avoid medication errors between NovoLog Mix 70/30 and any other insulin. The prescription for NovoLog Mix 70/30 should be written clearly in order to avoid confusion with other insulin products, for example, NovoLog or Novolin 70/30. In addition, the written prescription should clearly indicate the presentation, for example FlexPen or vial.

Date of Issue: May 7, 2010

Version: 9

Novo Nordisk®, NovoLog®, FlexPen®, and Novolin®, are trademarks owned by Novo Nordisk® A/S.

NovoLog® Mix 70/30 is covered by US Patent Nos. 5,547,930, 5,618,913, 5,834,422, 5,840,680, 5,866,538 and other patents pending.

FlexPen® is covered by US Patent Nos. 6,582,404, 6,004,297, 6,235,004 and other patents pending.

© 2002 – 2010 Novo Nordisk A/S

Manufactured by:

Novo Nordisk A/S

DK-2880 Bagsvaerd, Denmark

For information about NovoLog Mix 70/30 contact:

Novo Nordisk Inc.

Princeton, New Jersey 08540

1-800-727-6500

www.novonordisk-us.com

Relabeling of "Additional Barcode Label" by:
Physicians Total Care, Inc.
Tulsa, OK 74146

PATIENT INFORMATION

NovoLog® Mix 70/30

(NŌ-vō-log-MIX-SEV-en-tee-THIR-tee)

(70% insulin aspart protamine suspension and 30% insulin aspart injection, [rDNA origin])

Read the Patient Information leaflet that comes with NovoLog® Mix 70/30 before you start taking it and each time you get a refill. There may be new information. This leaflet does not take the place of talking with your healthcare provider about your diabetes or your treatment. Make sure you know how to manage your diabetes. Ask your healthcare provider if you have any questions about managing your diabetes.

What is NovoLog® Mix 70/30?

NovoLog® Mix 70/30 is a man-made insulin that is used to control high blood sugar in adults with diabetes mellitus.

It is not known if NovoLog® Mix 70/30 is safe or effective in children.

Who should not use NovoLog® Mix 70/30?

Do not take NovoLog® Mix 70/30 if:

- Your blood sugar is too low (hypoglycemia)
- You are allergic to any of the ingredients in NovoLog® Mix 70/30. See the end of this leaflet for a complete list of ingredients in NovoLog® Mix 70/30. Check with your healthcare provider if you are not sure.

What should I tell my healthcare provider before taking NovoLog® Mix 70/30?

Before you use NovoLog® Mix 70/30, tell your healthcare provider if you:

- have kidney or liver problems
- have any other medical conditions. Medical conditions can affect your insulin needs and your dose of NovoLog® Mix 70/30.
- are pregnant or plan to become pregnant. It is not known if NovoLog® Mix 70/30 will harm your unborn baby. Talk to your healthcare provider if you are pregnant or plan to become pregnant. You and your healthcare provider should decide about the best way to manage your diabetes while you are pregnant.
- are breastfeeding or plan to breastfeed. It is not known if NovoLog® Mix 70/30 passes into your breast milk. You and your healthcare provider should decide if you will take NovoLog® Mix 70/30 while you breastfeed.

Tell your healthcare provider about all medicines you take, including prescriptions and non-prescription medicines, vitamins and herbal supplements.

NovoLog® Mix 70/30 may affect the way other medicines work, and other medicines may affect how NovoLog® Mix 70/30 works. Your NovoLog® Mix 70/30 dose may change if you take other medicines.

Know the medicines you take. Keep a list of your medicines with you to show your healthcare providers and pharmacist when you get a new medicine.

How should I take NovoLog® Mix 70/30?

- Take NovoLog® Mix 70/30 exactly as your healthcare provider tells you to take it.
- Your healthcare provider will tell you how much NovoLog® Mix 70/30 to take and when to take it.
- Do not make any changes to your dose or type of insulin unless your healthcare provider tells you to.
- NovoLog Mix 70/30 starts acting fast. If you have Type 1 diabetes, inject it up to 15 minutes before you eat a meal. Do not inject NovoLog® Mix 70/30 if you are not planning to eat within 15 minutes.
- If you have Type 2 diabetes, you may inject NovoLog® Mix 70/30 up to 15 minutes before or after starting your meal.
- Do Not mix NovoLog® Mix 70/30 with other insulin products.
- Do Not use NovoLog® Mix 70/30 in an insulin pump.
- Inject NovoLog® Mix 70/30 under the skin (subcutaneously) of your stomach area, upper arms, buttocks or upper legs. NovoLog® Mix 70/30 may affect your blood sugar levels faster if you inject it under the skin of your stomach area. Never inject NovoLog® Mix 70/30 into a vein or into a muscle.
- Change (rotate) injection sites within the area you choose with each dose. Do not inject into the exact same spot for each injection.
- Read the instructions for use that come with your NovoLog® Mix 70/30. Talk to your healthcare provider if you have any questions. Your healthcare provider should show you how to inject NovoLog® Mix 70/30 before you start using it.
- NovoLog® Mix 70/30 comes in:
  - 10 mL vials for use with a syringe
  - 3 mL NovoLog® Mix 70/30 FlexPen®
- If you take too much NovoLog® Mix 70/30, your blood sugar may fall too low (hypoglycemia). You can treat mild low blood sugar (hypoglycemia) by drinking or eating something sugary right away (fruit juice, sugar candies, or glucose tablets). It is important to treat low blood sugar (hypoglycemia) right away because it could get worse and you could pass out (loss of consciousness).
- If you forget to take your dose of NovoLog® Mix 70/30, your blood sugar may go too high (hyperglycemia). If high blood sugar (hyperglycemia) is not treated it can lead to serious problems, like passing out (loss of consciousness), coma or even death. Follow your healthcare provider’s instructions for treating high blood sugar. Know your symptoms of high blood sugar which may include:

- increased thirst

- a hard time breathing

- frequent urination

- fruity smell on the breath

- drowsiness

- high amounts of sugar and ketones in your urine

- loss of appetite

- nausea, vomiting (throwing up) or stomach pain

- Do not share needles, insulin pens or syringes with others.
- Check your blood sugar levels. Ask your healthcare provider what your blood sugars should be and when you should check your blood sugar levels.

Your insulin dosage may need to change because of:

- illness

- change in diet

- stress

- change in physical activity or exercise

- other medicines you take

See the end of this patient information for instructions about preparing and giving your injection.

What should I consider while using NovoLog® Mix 70/30?

- Alcohol. Drinking alcohol may affect your blood sugar when you take NovoLog® Mix 70/30.
- Driving and operating machinery. You may have trouble paying attention or reacting if you have low blood sugar (hypoglycemia). Be careful when you drive a car or operate machinery. Ask your healthcare provider if it is alright for you to drive if you often have:
  - low blood sugar
  - decreased or no warning signs of low blood sugar

What are the possible side effects of NovoLog® Mix 70/30?

NovoLog® Mix 70/30 may cause serious side effects, including:

- low blood sugar (hypoglycemia). Symptoms of low blood sugar may include:

- sweating

- trouble concentrating or confusion

- dizziness or lightheadedness

- blurred vision

- shakiness

- slurred speech

- hunger

- anxiety, irritability or mood changes

- fast heart beat

- headache

- tingling of lips and tongue

Very low blood sugar can cause you to pass out (loss of consciousness), seizures, and death. Talk to your healthcare provider about how to tell if you have low blood sugar and what to do if this happens while taking NovoLog® Mix 70/30. Know your symptoms of low blood sugar. Follow your healthcare provider’s instructions for treating low blood sugar.

Talk to your healthcare provider if low blood sugar is a problem for you. Your dose of NovoLog® Mix 70/30 may need to be changed.

- Low potassium in your blood (hypokalemia)
- Reactions at the injection site (local allergic reaction). You may get redness, swelling, and itching at the injection site. If you keep having skin reactions or they are serious talk to your healthcare provider.
- Serious allergic reaction (whole body reaction). Get medical help right away, if you have any of these symptoms of an allergic reaction:
  - a rash over your whole body
  - have trouble breathing
  - a fast heartbeat
  - sweating
  - feel faint

The most common side effects of NovoLog® Mix 70/30 include:

- Skin thickening or pits at the injection site (lipodystrophy). Change (rotate) where you inject your insulin to help to prevent these skin changes from happening. Do not inject insulin into this type of skin.
- Weight gain
- Swelling of your hands and feet
- Vision changes

These are not all of the possible side effects from NovoLog® Mix 70/30. Ask your healthcare provider or pharmacist for more information.

Call your doctor for medical advice about side effects. You may report side effects to FDA at 1-800-FDA-1088.

How should I store NovoLog® Mix 70/30?

All Unopened NovoLog® Mix 70/30:

- Keep all unopened NovoLog® Mix 70/30 in the refrigerator between 36°F to 46°F (2°C to 8°C).
- Do not freeze or store next to the refrigerator cooling element. Do not use NovoLog® Mix 70/30 if it has been frozen.
- Keep unopened NovoLog® Mix 70/30 in the carton to protect from light.
- Unopened vials can be used until the expiration date on the NovoLog® Mix 70/30 label, if the medicine has been stored in a refrigerator.
- Unused NovoLog® Mix 70/30 FlexPen® can be used until the expiration date on the NovoLog® Mix 70/30 FlexPen® label, if the medicine has been stored in a refrigerator.

After NovoLog® Mix 70/30 has been opened:

- Vials
  - Keep in the refrigerator or at room temperature below 86°F (30°C) for up to 28 days.
  - Keep vials away from direct heat or light.
  - Throw away an opened vial after 28 days of use, even if there is insulin left in the vial.

- NovoLog® Mix 70/30 FlexPen®
  - Keep at room temperature below 86°F (30°C) for up to 14 days.
  - Do not store a NovoLog® Mix 70/30 FlexPen® that you are using in the refrigerator.
  - Keep NovoLog® Mix 70/30 FlexPen® away from direct heat or light.
  - Throw away a used NovoLog® Mix 70/30 FlexPen® after 14 days, even if there is insulin left in the syringe.

Never use insulin after the expiration date that is printed on the label and carton.

Keep NovoLog® Mix 70/30 and all medicines out of the reach of children.

General advice about NovoLog® Mix 70/30

Medicines are sometimes prescribed for conditions that are not mentioned in the patient leaflet. Do not use NovoLog® Mix 70/30 for a condition for which it was not prescribed. Do not give NovoLog® Mix 70/30 to other people, even if they have the same symptoms you have. It may harm them.

This leaflet summarizes the most important information about NovoLog® Mix 70/30. If you would like more information about NovoLog® Mix 70/30 or diabetes, talk with your healthcare provider. You can ask your healthcare provider or pharmacist for information about NovoLog® Mix 70/30 that is written for healthcare professionals. For more information call 1-800-727-6500 or go to www.novonordisk-us.com.

What are the ingredients in NovoLog® Mix 70/30?

- Active Ingredients NovoLog® Mix 70/30 FlexPen® and Vial: 70% Insulin aspart protamine suspension and 30% insulin aspart injection (rDNA origin).
- Inactive Ingredients NovoLog® Mix 70/30 FlexPen®: glycerol, phenol, metacresol, zinc, disodium hydrogen phosphate dihydrate, sodium chloride, protamine sulfate, water for injection, hydrochloric acid or sodium hydroxide.
- Inactive Ingredients NovoLog® Mix 70/30 Vial: mannitol, phenol, metacresol, zinc, disodium hydrogen phosphate dihydrate, sodium chloride, protamine sulfate, water for injection, hydrochloric acid or sodium hydroxide.

All NovoLog® Mix 70/30 vials and NovoLog® Mix 70/30 FlexPen® are latex free.

Helpful information for people with diabetes is published by the American Diabetes Association, 1701 N Beauregard Street, Alexandria, VA 22311 and is available www.diabetes.org.

Date of Issue: May 7, 2010

Version: 7

NovoLog®, FlexPen®, NovoFine®, are trademarks of Novo Nordisk A/S.

NovoLog® is covered by US Patent Nos. 5,547,930, 5,618,913, 5,834,422, 5,840,680, 5,866,538 and other patents pending.

FlexPen® is covered by US Patent Nos. 6,582,404, 6,004,297, 6,235,004 and other patents pending.

© 2002-2010 Novo Nordisk A/S

Manufactured by:

Novo Nordisk A/S

DK-2880 Bagsvaerd, Denmark

For information about NovoLog Mix 70/30® contact:

Novo Nordisk Inc.

100 College Road West

Princeton, New Jersey 08540

PATIENT INSTRUCTIONS FOR USE

NovoLog® Mix 70/30 10 mL vial (100 Units/mL, U-100)

Read the following Patient Instructions for Use carefully before you start using your NovoLog® Mix 70/30 10mL vial and each time you get a refill. There may be new information. You should read the instructions even if you have used NovoLog® Mix 70/30 10mL vials before.

Before starting, gather all of the supplies that you will need to use for preparing and giving your insulin injection.

Never re-use syringes and needles.

How should I prepare and deliver the injection using the NovoLog® Mix 70/30 10 mL vial?

1. Check to make sure you have the correct type of insulin. This is especially important if you use different types of insulin.
2. Look at the vial and the insulin. The insulin should be white and cloudy after mixing. The tamper-resistant cap should be on the vial before the first use. If the cap has already been removed before your first use of the vial, or if the insulin looks clear or contains any particles, do not use it and return it to your pharmacy.
3. Wash your hands with soap and water. Clean your injection site with an alcohol swab and let the injection site dry before you inject. Talk with your healthcare provider about how to rotate injection sites and how to give an injection.
4. If you are using a new vial, pull off the tamper-resistant cap. Wipe the rubber stopper with an alcohol swab.
5. Roll the vial gently 10 times in your hands to mix it. This should be done with the vial in a horizontal (flat) position between your palms. Do not shake the vial. Shaking right before the dose is drawn into the syringe may cause bubbles or foam. This can cause you to draw up the wrong dose of insulin. The insulin should be used only if it looks white and cloudy.
6. Pull back the plunger on the syringe until the black tip reaches the marking for the number of units you will inject.
7. Push the needle through the rubber stopper into the vial, and push the plunger all the way in to force air into the vial.
8. Turn the vial and syringe upside down and slowly pull the plunger back to a few units beyond the correct dose needed.
9. If there are air bubbles in the syringe, tap the syringe gently with your finger to raise the air bubbles to the top. Slowly push the plunger to the marking for your dose. This should move any air bubbles in the syringe back into the vial.
10. Check to make sure you have the right dose of NovoLog® Mix 70/30 in the syringe.
11. Pull the syringe out of the vial’s rubber stopper.
12. If there is a delay after you rolled the vial, you will have to roll it again to remix the insulin and redraw your medicine. Your healthcare provider should tell you if you need to pinch the skin before inserting the needle. This can be different from person to person so it is important to ask your doctor if you did not receive instructions on pinching the skin. Insert the needle into the skin right away. Push the plunger to inject the insulin under your skin. Keep the needle under your skin for at least 6 seconds to make sure you have injected all the insulin. When you are finished injecting the insulin, pull the needle out of your skin.
13. Your may see a drop of NovoLog® Mix 70/30 at the needle tip. This is normal and has no effect on the dose you just received. If blood appears after you pull the needle from your skin, press the injection site lightly with an alcohol swab. Do not rub the area. Do not recap the needle.
14. After the injection, dispose of the needle and syringe in a puncture-resistant container. Place used syringes, needles, and insulin vials in a disposable puncture-resistant sharps container, or some type of hard plastic or metal container with a screw on cap such as a detergent bottle or coffee can.
15. Ask your healthcare provider about the right way to throw away used syringes and needles. There may be state or local laws about the right way to throw away used syringes and needles. Do not throw away used needles and syringes in household trash or recycling bins.

Helpful information for people with diabetes is published by the American Diabetes Association, 1701 N. Beauregard Street, Alexandria, VA 22311.

Date of Issue: May 7, 2010

Version: 6

Novo Nordisk®, NovoLog®, FlexPen® and NovoFine® are trademarks owned by Novo Nordisk A/S.

© 2002–2010 Novo Nordisk A/S

NovoLog® Mix 70/30 is covered by US Patent Nos. 5,547,930, 5,618,913, 5,834,422, 5,840,680, 5,866,538 and other patents pending.

For information about NovoLog® Mix 70/30 contact:

Novo Nordisk Inc.

100 College Road West

Princeton, New Jersey 08540

1-800-727-6500

www.novonordisk-us.com

Manufactured by:

Novo Nordisk A/S

DK-2880 Bagsvaerd, Denmark

PATIENT INSTRUCTIONS FOR USE

NovoLog® Mix 70/30 FlexPen®

Read the following instructions carefully before you start using your NovoLog® Mix 70/30 FlexPen® and each time you get a refill. There may be new information. You should read the instructions even if you have used Novolog® Mix 70/30 FlexPen® before.

NovoLog® Mix 70/30 FlexPen® is a disposable dial-a-dose insulin pen. You can select doses from 1 to 60 units in increments of 1 unit. NovoLog® Mix 70/30 FlexPen® is designed to be used with NovoFine® needles.

NovoLog Mix® 70/30 FlexPen® should not be used by people who are blind or have severe visual problems without the help of a person who has good eyesight and who is trained to use the NovoLog® Mix 70/30 FlexPen® the right way.

Getting ready

Make sure you have the following items:

- NovoLog® Mix 70/30 FlexPen®
- New NovoFine® needle
- Alcohol swab

PREPARING YOUR NOVOLOG® MIX 70/30 FLEXPEN®

- Wash your hands with soap and water.
- Before you start to prepare your injection, check the label to make sure that you are taking the right type of insulin. This is especially important if you take more than 1 type of insulin. NovoLog® Mix 70/30 should look cloudy after mixing.

Before your first injection with a new NovoLog® Mix 70/30 FlexPen® you must mix the insulin:

A. Let the insulin reach room temperature before you use it. This makes it easier to mix.

Pull off the pen cap (see diagram A).

B. Roll the pen between your palms 10 times - it is important that the pen is kept horizontal (see diagram B).

C. Then gently move the pen up and down ten times between position 1 and 2 as shown, so the glass ball moves from one end of the cartridge to the other (see diagram C).

Repeat rolling and moving the pen until the liquid appears white and cloudy.

For every following injection move the pen up and down between positions 1 and 2 at least ten times until the liquid appears white and cloudy.

After mixing, complete all the following steps of the injection right away. If there is a delay, the insulin will need to be mixed again.

Wipe the rubber stopper with an alcohol swab.

Δ Before you inject, there must be at least 12 units of insulin left in the cartridge to make sure the remaining insulin is evenly mixed. If there are less than 12 units left, use a new NovoLog® Mix 70/30 FlexPen®.

Attaching the needle

D. Remove the protective tab from a disposable needle.

Screw the needle tightly onto your NovoLog® Mix 70/30 FlexPen®. It is important that the needle is put on straight (see diagram D).

Never place a disposable needle on your NovoLog® Mix 70/30 FlexPen® until you are ready to take your injection.

E. Pull off the big outer needle cap (see diagram E).

F. Pull off the inner needle cap and dispose of it (see diagram F).

Δ Always use a new needle for each injection to help ensure sterility and prevent blocked needles.

Δ Be careful not to bend or damage the needle before use.

Δ To reduce the risk of a needle stick, never put the inner needle cap back on the needle.

Giving the airshot before each injection

Before each injection small amounts of air may collect in the cartridge during normal use. To avoid injecting air and to make sure you take the right dose of insulin:

G. Turn the dose selector to select 2 units (see diagram G).

H. Hold your NovoLog® Mix 70/30 FlexPen® with the needle pointing up. Tap the cartridge gently with your finger a few times to make any air bubbles collect at the top of the cartridge (see diagram H).

I. Keep the needle pointing upwards, press the push-button all the way in (see diagram I). The dose selector returns to 0.

A drop of insulin should appear at the needle tip. If not, change the needle and repeat the procedure no more than 6 times.

If you do not see a drop of insulin after 6 times, do not use the NovoLog Mix® 70/30 FlexPen® and contact Novo Nordisk at 1-800-727-6500.

A small air bubble may remain at the needle tip, but it will not be injected.

SELECTING YOUR DOSE

Check and make sure that the dose selector is set at 0.

J. Turn the dose selector to the number of units you need to inject. The pointer should line up with your dose.

The dose can be corrected either up or down by turning the dose selector in either direction until the correct dose lines up with the pointer (see diagram J). When turning the dose selector, be careful not to press the push-button as insulin will come out.

You cannot select a dose larger than the number of units left in the cartridge.

You will hear a click for every single unit dialed. Do not set the dose by counting the number of clicks you hear.

Δ Do not use the cartridge scale printed on the cartridge to measure your dose of insulin.

GIVING THE INJECTION

Do the injection exactly as shown to you by your healthcare provider. Your healthcare provider should tell you if you need to pinch the skin before injecting. Wipe the skin with an alcohol swab and let the area dry.

K. Insert the needle into your skin.

Inject the dose by pressing the push-button all the way in until the 0 lines up with the pointer (see diagram K). Be careful only to push the button when injecting.

Turning the dose selector will not inject insulin.

L. Keep the needle in the skin for at least 6 seconds, and keep the push-button pressed all the way in until the needle has been pulled out from the skin (see diagram L). This will make sure that the full dose has been given.

You may see a drop of NovoLog® Mix 70/30 at the needle tip. This is normal and has no effect on the dose you just received. If blood appears after you take the needle out of your skin, press the injection site lightly with an alcohol swab. Do not rub the area.

After the injection

Do not recap the needle. Recapping can lead to a needle stick injury. Remove the needle from the NovoLog® Mix 70/30 FlexPen® after each injection. This helps to prevent infection, leakage of insulin, and will help to make sure you inject the right dose of insulin.

Δ Put the needle and any empty NovoLog® Mix 70/30 FlexPen® or any used NovoLog® Mix 70/30 FlexPen® still containing insulin in a sharps container or some type of hard plastic or metal container with a screw top such as a detergent bottle or empty coffee can. These containers should be sealed and thrown away the right way. Check with your healthcare provider about the right way to throw away used syringes and needles. There may be local or state laws about how to throw away used needles and syringes. Do not throw away used needles and syringes in household trash or recycling bins.

The NovoLog® Mix 70/30 FlexPen® prevents the cartridge from being completely emptied. It is designed to deliver 300 units.

M. Put the pen cap on the NovoLog® Mix 70/30 FlexPen® and store the NovoLog® Mix 70/30 FlexPen® without the needle attached (see diagram M).

FUNCTION CHECK

N. If your NovoLog® Mix 70/30 FlexPen® is not working the right way, follow the steps below:

- Screw on a new NovoFine® needle.
- Remove the big outer needle cap and the inner needle cap.
- Do an airshot as described in "Giving the airshot before each injection".
- Put the big outer needle cap onto the needle. Do not put on the inner needle cap.
- Turn the dose selector so the dose indicator window shows 20 units.
- Hold the NovoLog® Mix 70/30 FlexPen® so the needle is pointing down.
- Press the push-button all the way in.

The insulin should fill the lower part of the big outer needle cap (see diagram N). If NovoLog® Mix 70/30 FlexPen® has released too much or too little insulin, do the function check again. If the same problem happens again, do not use your NovoLog® Mix 70/30 FlexPen® and contact Novo Nordisk at 1-800-727-6500.

Maintenance

Your NovoLog® Mix 70/30 FlexPen® is designed to work accurately and safely. It must be handled with care. Avoid dropping your NovoLog® Mix 70/30 FlexPen® as it may damage it. If you are concerned that your NovoLog® Mix 70/30 FlexPen® is damaged, use a new one. You can clean the outside of your NovoLog® Mix 70/30 FlexPen® by wiping it with a damp cloth. Do not soak or wash your NovoLog® Mix 70/30 FlexPen® as it may damage it. Do not refill your NovoLog® Mix 70/30 FlexPen®.

Δ Remove the needle from the NovoLog® Mix 70/30 FlexPen® after each injection. This helps to ensure sterility, prevent leakage of insulin, and will help to make sure you inject the right dose of insulin for future injections.

Δ Be careful when handling used needles to avoid needle sticks and transfer of infectious diseases.

Δ Keep your NovoLog® Mix 70/30 FlexPen® and needles out of the reach of children.

Δ Use NovoLog® Mix 70/30 FlexPen® as directed to treat your diabetes. Needles and NovoLog® Mix 70/30 FlexPen® must not be shared.

Δ Always use a new needle for each injection.

Δ Novo Nordisk is not responsible for harm due to using this insulin pen with products not recommended by Novo Nordisk.

Δ As a precautionary measure, always carry a spare insulin delivery device in case your NovoLog® Mix 70/30 FlexPen® is lost or damaged.

Remember to keep the disposable NovoLog® Mix 70/30 FlexPen® with you. Do not leave it in a car or other location where it can get too hot or too cold.

Date of Issue: May 7, 2010

Version: 8

NovoLog® , FlexPen® , NovoFine® , are trademarks of Novo Nordisk A/S.

NovoLog® is covered by US Patent Nos. 5,547,930, 5,618,913, 5,834,422, 5,840,680, 5,866,538 and other patents pending.

FlexPen® is covered by US Patent Nos. 6,582,404, 6,004,297, 6,235,004 and other patents pending.

© 2002-2010 Novo Nordisk A/S

Manufactured by:

Novo Nordisk A/S

DK-2880 Bagsvaerd, Denmark

For information about NovoLog Mix 70/30® contact:

Novo Nordisk Inc.

100 College Road West,

Princeton, New Jersey 08540

PRINCIPAL DISPLAY PANEL

NovoLog® Mix 70/30

70% insulin aspart protamine

suspension and 30% insulin

aspart injection, (rDNA origin)

100 units/mL 10mL

NDC 54868-5201-0

Shake carefully before using. See enclosed insert for proper technique.

Rx only

U-100

------------------------------------------------------------------------------------------------------------------------------------------

NovoLog® Mix 70/30

FlexPen® Prefilled Syringe

70% insulin aspart protamine, suspension and

30% insulin aspart injection, (rDNA origin)

100 units/mL (U-100)

5x3 mL Prefilled Insulin Syringes

NDC 54868-5327-1

Rx only

Single patient use only

Shake carefully before using. See

enclosed insert for proper technique.

For use with NovoFine® disposable

needles.

Keep in a cold place.

Avoid freezing.

Protect from light.